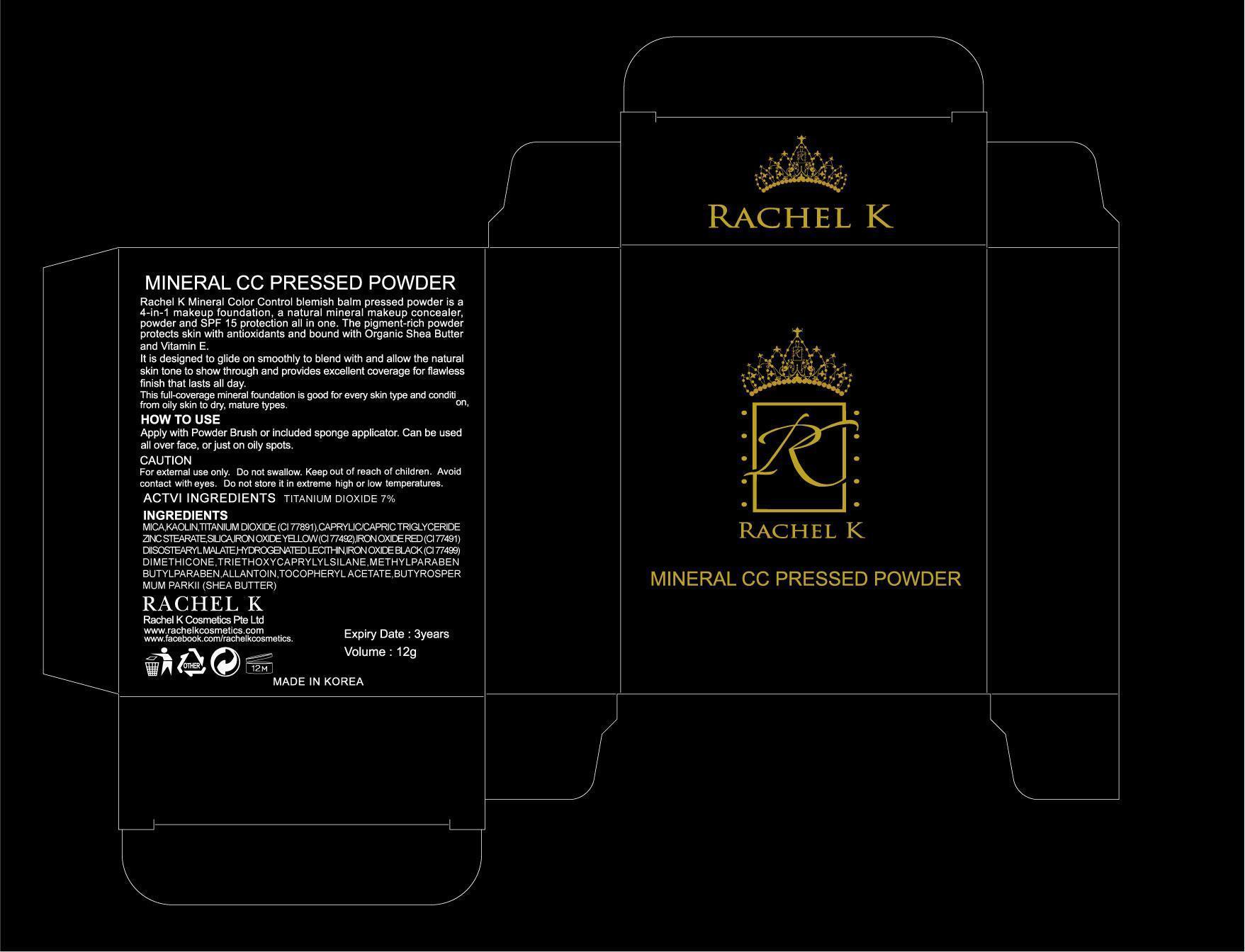 DRUG LABEL: RACHEL K MINERAL CC PRESSED
NDC: 53241-020 | Form: POWDER
Manufacturer: RACHEL K COSMETICS PTE. LTD.
Category: otc | Type: HUMAN OTC DRUG LABEL
Date: 20120920

ACTIVE INGREDIENTS: TITANIUM DIOXIDE 0.84 g/12 g
INACTIVE INGREDIENTS: KAOLIN; MEDIUM-CHAIN TRIGLYCERIDES; ZINC STEARATE; DIMETHICONE

ACTIVE INGREDIENT

Active ingredient: TITANIUM DIOXIDE 7%

INACTIVE INGREDIENT

Inactive ingredients:
MICA, KAOLIN, CAPRYLIC/CAPRIC TRIGLYCERIDE, ZINC STEARATE, SILICA, IRON OXIDE YELLOW, IRON OXIDE RED, DIISOSTEARYL MALATE, HYDROGENATED LECITHIN, IRON OXIDE BLACK, DIMETHICONE, TRIETHOXYCAPRYLYLSILANE, METHYLPARABEN, BUTYLPARABEN, ALLANTOIN, TOCOPHERYL ACETATE, BUTYROSPERMUM PARKII (SHEA BUTTER)

PURPOSE

Purpose: Sunscreen

WARNINGS

Caution:
For external use only.
Do not swallow.
Keep out of reach of children.
Avoid contact with eyes.
Do not store it in extreme high or low temperatures.

KEEP OUT OF REACH OF CHILDREN

INDICATIONS AND USAGE

HOW TO USE:
Apply with Powder Brush or included sponge applicator.
Can be used all over face, or just on oily spots.

DOSAGE AND ADMINISTRATION

HOW TO USE:
Apply with Powder Brush or included sponge applicator.
Can be used all over face, or just on oily spots.